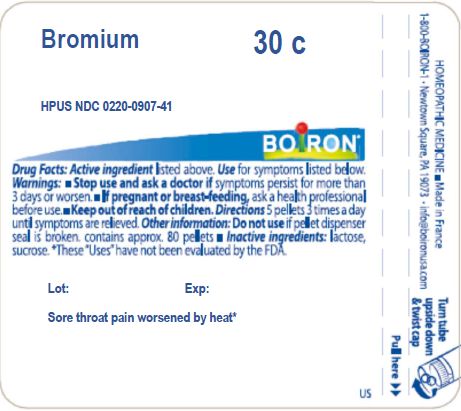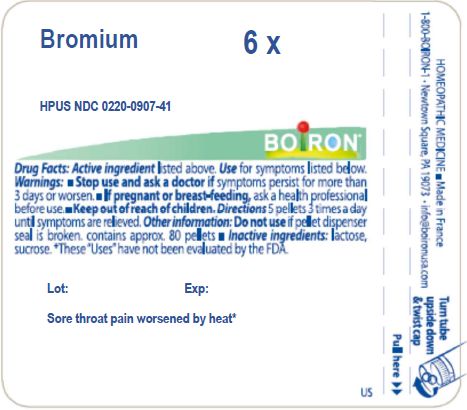 DRUG LABEL: Bromium
NDC: 0220-0907 | Form: PELLET
Manufacturer: Boiron
Category: homeopathic | Type: HUMAN OTC DRUG LABEL
Date: 20231109

ACTIVE INGREDIENTS: BROMINE 6 [hp_X]/6 [hp_X]
INACTIVE INGREDIENTS: LACTOSE, UNSPECIFIED FORM; SUCROSE

Bromium

ACTIVE INGREDIENT

BROMIUM HPUS

6X 6C 30C

INDICATIONS AND USAGE

Sore throat pain worsened by heat*

STOP USE AND SEE A DOCTOR IF SYMPTOMS PERSIST FOR MORE THAN 3 DAYS OR WORSEN

PREGNANCY OR BREAST FEEDING

IF PREGNANT OR BREAST-FEEDING ASK A HEALTH PROFESSIONAL BEFORE USE

KEEP OUT OF REACH OF CHILDREN

DOSAGE AND ADMINISTRATION

5 PELLETS 3 TIMES A DAY UNTIL SYMPTOMS ARE RELIEVED

DO NOT USE IF PELLET DISPENSER SEAL IS BROKEN

CONTAINS APPROX 80 PELLETS

INACTIVE INGREDIENT

LACTOSE, SUCROSE

QUESTIONS

1-800-BOIRON-1

Newtown Square, PA 19073-3267

info@boironusa.com

These "uses" have not been evaluated by the FDA